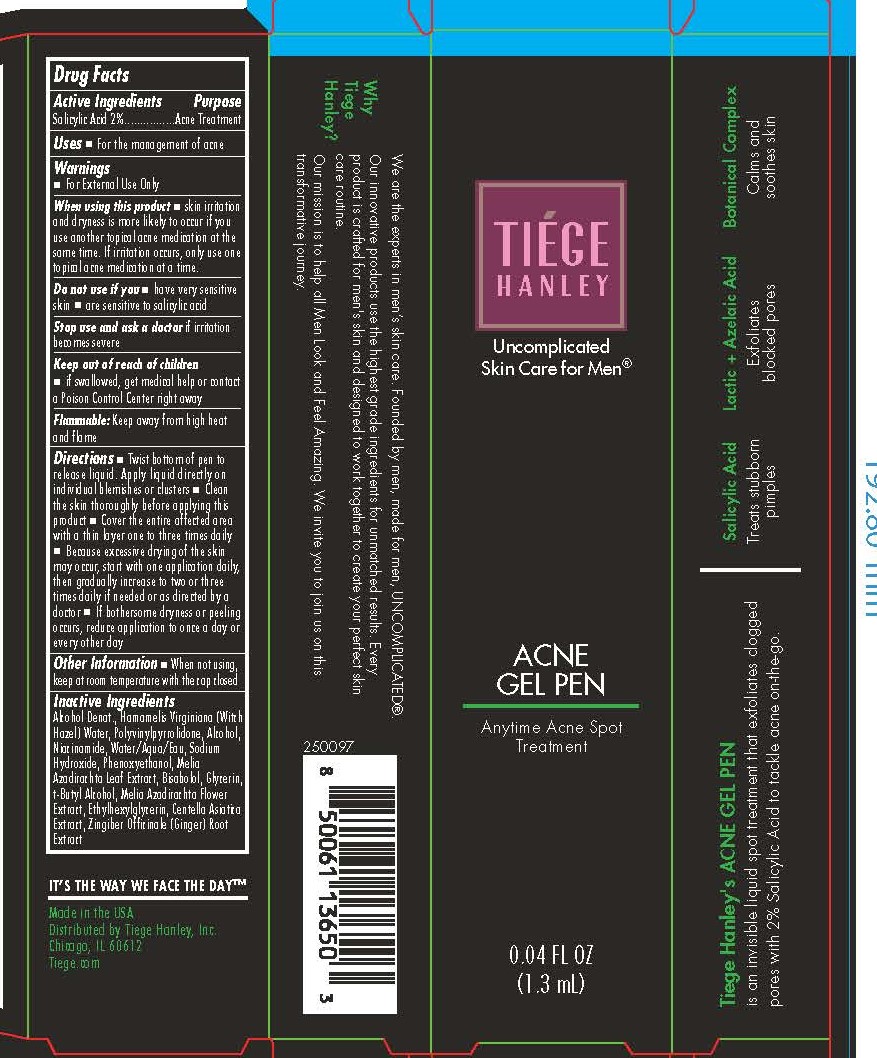 DRUG LABEL: Acne Gel Pen
NDC: 71714-004 | Form: GEL
Manufacturer: Tiege Hanley
Category: otc | Type: HUMAN OTC DRUG LABEL
Date: 20251018

ACTIVE INGREDIENTS: SALICYLIC ACID 20 mg/1 mL
INACTIVE INGREDIENTS: ZINGIBER OFFICINALE (GINGER) ROOT OIL; NIACINAMIDE; SODIUM HYDROXIDE; MELIA AZADIRACHTA LEAF; PVP; WATER; PHENOXYETHANOL; GLYCERIN; HAMAMELIS VIRGINIANA LEAF WATER; T-BUTYL ALCOHOL; AZADIRACHTA INDICA FLOWER; ALCOHOL; BISABOLOL; ETHYLHEXYLGLYCERIN; CENTELLA ASIATICA

Acne Gel Pen

Keep out of reach of children
■ if swallowed, get medical help or contact
a Poison Control Center right away

DOSAGE AND ADMINISTRATION

Directions ■ Twist bottom of pen to
release liquid. Apply liquid directly on
individual blemishes or clusters ■ Clean
the skin thoroughly before applying this
product ■ Cover the entire affected area
with a thin layer one to three times daily
■ Because excessive drying of the skin
may occur, start with one application daily,
then gradually increase to two or three
times daily if needed or as directed by a
doctor ■ If bothersome dryness or peeling
occurs, reduce application to once a day or
every other day

Purpose.......Acne Treatment

ACTIVE INGREDIENT

Salicylic Acid 2%

Stop use and ask a doctor if irritation
becomes severe.

Inactive Ingredients:
Alcohol Denat., Hamamelis Virginiana (Witch
Hazel) Water, Polyvinylpyrrolidone, Alcohol,
Niacinamide, Water/Aqua/Eau, Sodium
Hydroxide, Phenoxyethanol, Melia
Azadirachta Leaf Extract, Bisabolol, Glycerin,
t-Butyl Alcohol, Melia Azadirachta Flower
Extract, Ethylhexylglycerin, Centella Asiatica
Extract, Zingiber Officinale (Ginger) Root
Extract

INDICATIONS AND USAGE

Uses ■ For the management of acne

Warnings
■ For External Use Only

When using this product ■ skin irritation
and dryness is more likely to occur if you
use another topical acne medication at the
same time. If irritation occurs, only use one
topical acne medication at a time.
Do not use if you ■ have very sensitive
skin ■ are sensitive to salicylic acid
Stop use and ask a doctor if irritation
becomes severe
Keep out of reach of children
■ if swallowed, get medical help or contact
a Poison Control Center right away

Flammable: Keep away from high heat
and flame